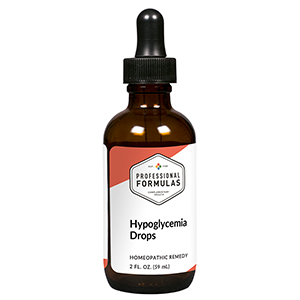 DRUG LABEL: Glucose Drops
NDC: 63083-2031 | Form: LIQUID
Manufacturer: Professional Complementary Health Formulas
Category: homeopathic | Type: HUMAN OTC DRUG LABEL
Date: 20190815

ACTIVE INGREDIENTS: CHROMIUM 2 [hp_X]/59 mL; OXOGLURIC ACID 3 [hp_X]/59 mL; CORN SYRUP 6 [hp_X]/59 mL; FRUCTOSE 6 [hp_X]/59 mL; MOMORDICA BALSAMINA WHOLE 6 [hp_X]/59 mL; BOS TAURUS PANCREAS 6 [hp_X]/59 mL; PYRIDOXINE 6 [hp_X]/59 mL; SUCROSE 6 [hp_X]/59 mL; VANADIUM 6 [hp_X]/59 mL; MANGANESE GLUCONATE 8 [hp_X]/59 mL; LYCOPODIUM CLAVATUM SPORE 9 [hp_X]/59 mL; MANDRAGORA OFFICINARUM ROOT 9 [hp_X]/59 mL; PHOSPHORIC ACID 12 [hp_X]/59 mL; GONORRHEAL URETHRAL SECRETION HUMAN 30 [hp_X]/59 mL
INACTIVE INGREDIENTS: ALCOHOL; WATER

C31

ACTIVE INGREDIENTS

Chromium muriaticum 2X
Alpha ketoglutaric acid 3X
Corn syrup 6X
Fructose 6X
Momordica balsamina 6X
Pancreas 6X
Pyridoxine 6X
Sucrose 6X
Vanadium metallicum 6X
Manganum gluconate 8X
Lycopodium clavatum 9X
Mandragora officinarum 9X
Phosphoricum acidum 12X
Medorrhinum 30X

QUESTIONS

Professional Formulas

PO Box 2034 Lake Oswego, OR 97035

INDICATIONS

For the temporary relief of excess sweating, increased hunger, fatigue, or lightheadedness.*

PURPOSE

*Claims based on traditional homeopathic practice, not accepted medical evidence. Not FDA evaluated.

WARNINGS

Consult a doctor if condition worsens or if symptoms persist. Keep out of the reach of children. In case of overdose, get medical help or contact a poison control center right away. If pregnant or breastfeeding, ask a healthcare professional before use.

Keep out of the reach of children.

PREGNANCY OR BREAST FEEDING

If pregnant or breastfeeding, ask a healthcare professional before use.

DIRECTIONS

Place drops under tongue 30 minutes before/after meals. Adults and children 12 years and over: Take 10 drops up to 3 times per day for up to 6 weeks. For immediate onset of symptoms, take 10 to 15 drops every 15 minutes up to 3 hours. For less severe symptoms, take 10-15 drops hourly up to 8 hours. Consult a physician for use in children under 12 years of age.

OTHER INFORMATION

Tamper resistant. If seal is broken, do not use. After opening, close container tightly and store at room temperature away from heat.

INACTIVE INGREDIENTS

20% ethanol, purified water.

LABEL

Est 1985

Professional Formulas

Complementary Health

Glucose Drops

Homeopathic Remedy

2 FL. OZ. (59 mL)